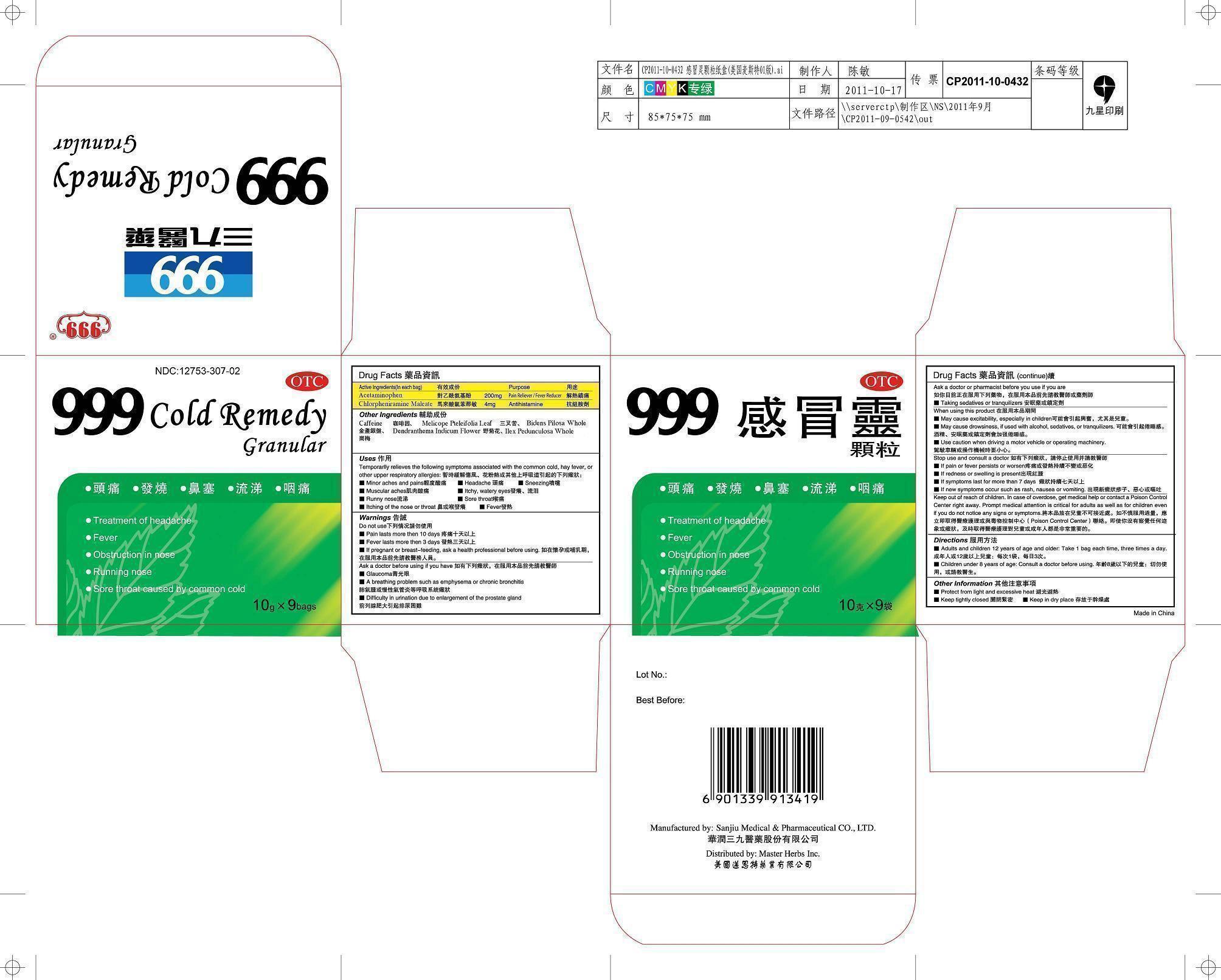 DRUG LABEL: 999 COLD REMEDY GRANULAR
NDC: 12753-307 | Form: GRANULE
Manufacturer: China Resources Sanjiu Medical & Pharmaceutical Co Ltd
Category: otc | Type: HUMAN OTC DRUG LABEL
Date: 20130924

ACTIVE INGREDIENTS: Acetaminophen 200 mg/90 g; Chlorpheniramine Maleate 4 mg/90 g
INACTIVE INGREDIENTS: Caffeine; MELICOPE PTELEIFOLIA LEAF; Bidens Pilosa Whole; Dendranthema indicum flower; ilex Pedunculosa whole

999 COLD REMEDY GRANULAR

Active Ingredients

Acetaminophen 200 mg

Chlorpheniramine Maleate 4 mg

Purpose

Acetaminophen Pain Reliever/Fever Reducer

Chlorpheniramine Maleate Antihistamine

Uses

Temporarily relieves the following symptoms associated with the common cold, hay fever, or other upper respiratory allergies:

minor achies and pains

headache

sneezing

musclular aches

itchy, watery eyes

sore throat

running nose

fever

itching of the nose or throat

Warnings

Do not use if

pain lasts more than 10 days

fever lasts more than 3 days

Ask a doctor before using if you have

Glaucoma

A breathing problem such as emphysema or chronic bronchitis

Difficulty in urination due to enlargement of the prostate gland

Taking sedatives or tranquilizers

As a doctor or pharmacist before you use if you are

Taking sedatives or transquilizers

When using this product

may cause excitability, especially in children

may cause drowsiness, if used with alcohol, sedatives or transquilizers

use caution when driving a motor vehicle or operating machinery

Stop use and consult a doctor

if pain or fever persists or worsen

if redness or swelling is present

if symptoms last for more than 7 days

if new symptoms occur such as rash, mausea or vomiting

Warnings

If pregnant or beasting-feeding, ask a health professional before using.

Stop use and consult a doctor

Keep out of reach of children. In case of overdose, get medical help or contact a Poison Control Center right away. Prompt medical attention is critical for adults as well as children even if you do not notice any signs or symptoms.

Directions

Adults and children 12 years of age and older: take a capsules each time, three times a day.

Children under 8 years of age: consult a doctor before using.

Other information

Protect from light and excessive heat

Keep tightly closed

Keep in a dry place

Other Ingredients

Caffeine

Melicope Pteleifolia Leaf

Bidens Pilosa

Dendranthema Indicum Flower

Ilex Peduunculosa Whole